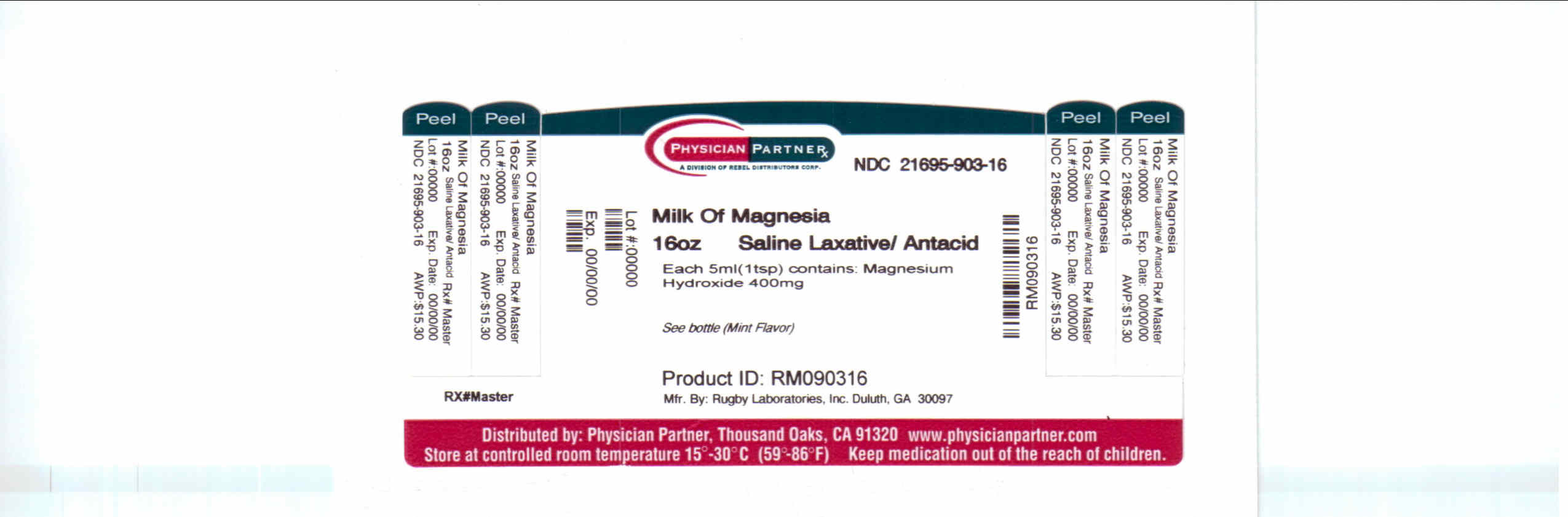 DRUG LABEL: Magnesium Hydroxide
NDC: 21695-903 | Form: LIQUID
Manufacturer: Rebel Distributors Corp
Category: otc | Type: HUMAN OTC DRUG LABEL
Date: 20110221

ACTIVE INGREDIENTS: MAGNESIUM HYDROXIDE 400 mg/5 mL
INACTIVE INGREDIENTS: WATER; SACCHARIN SODIUM; SODIUM HYPOCHLORITE

Milk of Magnesia Drug Facts

Active ingredient

Magnesium Hydroxide 400mg

Purpose

Saline Laxative / Antacid

Keep Out of Reach of Children

In case of overdose, get medical help or contact a Poison Control Center right away.

Uses

Laxative: relieves occasional constipation; generally produces a bowel movement in 1/2 to 6 hours.

Antacid: relieves heartburn, sour stomach & acid indigestion.

Warnings

Ask a doctor before use if you have:

° kidney disease ° a magnesium-restricted diet ° stomach pain, nausea or vomiting ° a sudden change in bowel habits that lasts over 2 weeks

Ask a doctor or pharmacist before use if you are taking any other drug.

° antacids may interact with certain prescription drugs ° laxatives may affect how other drugs work, so should be taken 2 or more hours before or after other drugs.

When using this product as an antacid, it may have a laxative effect.

Stop use and ask a doctor if ° you have rectal bleeding or no bowel movement after using this product. These could be signs of a serious condition ° You need to use a laxative for more than 1 week ° symptoms last more than 2 weeks.

If pregnant or breast-feeding, ask a health professional before use.

Other Information

each 5 mL teaspoon contains: magnesium 165mg and sodium 2 mg

store at room temperature

protect from freezing

keep tightly closed

Directions

Laxative: ° shake well before using

° drink a full glass (8 ounces) of liquid with each dose

° may be taken as a single or divided dose

Antacid: ° do not take more than 12 teaspoons in 24 hours

° do not use maximum dosage for more than 2 weeks

Laxative:

adults and children 12 years and older: 2 to 4 tablespoons

children 6 to under 12 years: 1 to 2 tablespoons

children 2 to under 6 years: 1 to 3 teaspoons

children under 2 years: ask a doctor

Antacid:

adults and children 12 years and older: 1 to 3 teaspoons with water, up to 4 times daily

children under 12 years: ask a doctor

Inactive ingredients

flavor, purified water, saccharin sodium, sodium hypochlorite

Questions or comments? Call 1-800-645-2158, 9 am - 5 pm EST, Monday-Friday